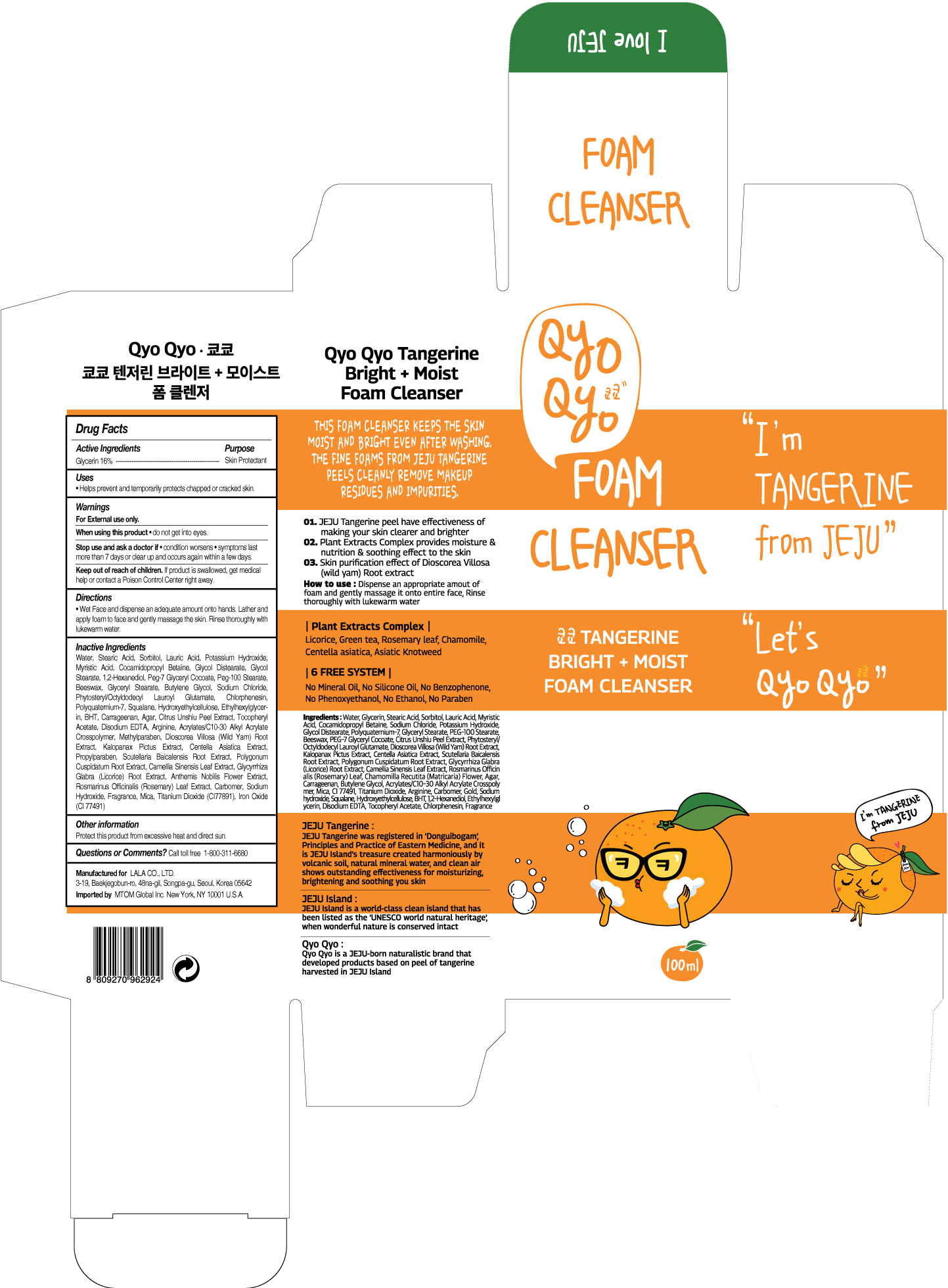 DRUG LABEL: QYO QYO Tangerine Bright Moist Foam Cleanser
NDC: 71733-105 | Form: LIQUID
Manufacturer: LaLa Co., Ltd.
Category: otc | Type: HUMAN OTC DRUG LABEL
Date: 20190101

ACTIVE INGREDIENTS: GLYCERIN 16 g/100 mL
INACTIVE INGREDIENTS: STEARIC ACID; TANGERINE PEEL; WATER; LAURIC ACID

Qyo Qyo Tangerine Bright + Moist
Foam Cleanser

ACTIVE INGREDIENTS

GLYCERIN 16%

PURPOSE

SKIN PROTECTANT

USES

- Helps prevent and temporarily protects chapped or cracked skin.

WARNINGS

For external use only.

When using this product • do not get into eyes.

STOP USE

Stop us and ask doctor if • condition worsens • symptoms last
more than 7 days or clear up and occurs again within a few days.

Keep out of reach of children. If product is swallowed, get medical help or contact a Poison Control Center right away.

Directions

• Wet Face and dispense an adequate amount onto hands. Lather and apply foam to face and gently massage the skin. Rinse thoroughly with lukewarm water.

Inactive Ingredients

Water, Stearic Acid, Sorbitol, Lauric Acid, Potassium Hydroxide, Myristic Acid, Cocamidopropyl Betaine, Glycol Distearate, Glycol Stearate, 1,2-Hexanediol, Peg-7 Glyceryl Cocoate, Peg-100 Stearate, Beeswax, Glyceryl Stearate, Butylene Glycol, Sodium Chloride, Phytosteryl/Octyldodecyl Lauroyl Glutamate, Chlorphenesin, Polyquaternium-7, Squalane, Hydroxyethylcellulose, Ethylhexylglycerin, BHT, Carrageenan, Agar, Citrus Unshiu Peel Extract, Tocopheryl Acetate, Disodium EDTA, Arginine, Acrylates/C10-30 Alkyl Acrylate Crosspolymer, Methylparaben, Dioscorea Villosa (Wild Yam) Root Extract, Kalopanax Pictus Extract, Centella Asiatica Extract, Propylparaben, Scutellaria Baicalensis Root Extract, Polygonum Cuspidatum Root Extract, Camellia Sinensis Leaf Extract, Glycyrrhiza Glabra (Licorice) Root Extract, Anthemis Nobilis Flower Extract, Rosmarinus Officinalis (Rosemary) Leaf Extract, Carbomer, Sodium Hydroxide, Fragrance, Mica, Titanium Dioxide (CI77891), Iron Oxide (CI 77491)

Other Information

Protect this product from excessive heat and direct sun.

Questions or Comments?

Call toll free 1-800-311-6680